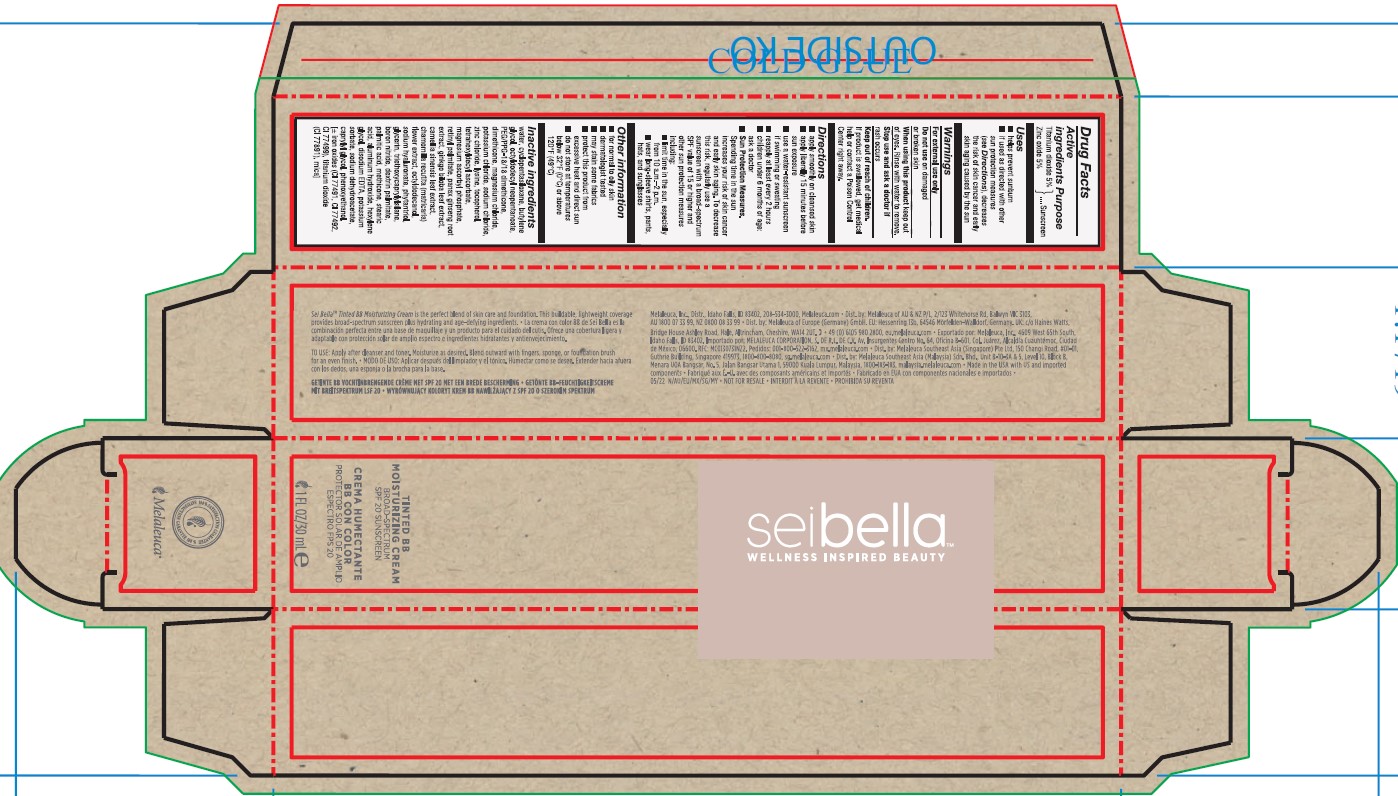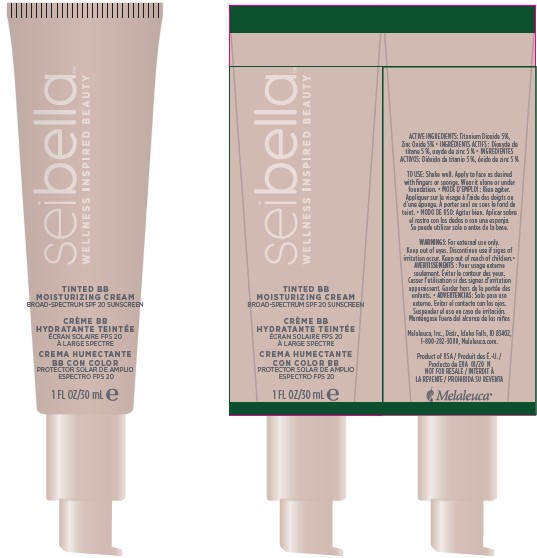 DRUG LABEL: Sei Bella Tinted BB Moisturizing Cream
NDC: 59735-891 | Form: LOTION
Manufacturer: Mana Products Inc.
Category: otc | Type: HUMAN OTC DRUG LABEL
Date: 20250328

ACTIVE INGREDIENTS: ZINC OXIDE 1.5 g/30 mL; TITANIUM DIOXIDE 1.5 g/30 mL
INACTIVE INGREDIENTS: CAMELLIA SINENSIS LEAF; TETRAHEXYLDECYL ASCORBATE; BUTYLENE GLYCOL; SODIUM CHLORIDE; LYSINE; FERROSOFERRIC OXIDE; RETINYL PALMITATE; SODIUM HYALURONATE; CYCLOPENTASILOXANE; MATRICARIA CHAMOMILLA; BORON NITRIDE; STEARIC ACID; DEXTRIN PALMITATE (CORN; 20000 MW); PANAX GINSENG ROOT OIL; TRIETHOXYCAPRYLYLSILANE; MAGNESIUM ASCORBYL PHOSPHATE; SODIUM DEHYDROACETATE; TOCOPHEROL; METHICONE (20 CST); ALUMINUM HYDROXIDE; GLYCERIN; OCTYLDODECYL NEOPENTANOATE; POTASSIUM SORBATE; PALMITIC ACID; WATER; FERRIC OXIDE YELLOW; POTASSIUM CHLORIDE; ZINC CHLORIDE; PEG/PPG-18/18 DIMETHICONE; MAGNESIUM CHLORIDE; DIMETHICONE; MICA; FERRIC OXIDE RED; HEXYLENE GLYCOL; PHENOXYETHANOL; EDETATE DISODIUM; GINKGO BILOBA LEAF OIL; PHYTANTRIOL; CAPRYLYL GLYCOL

ACTIVE INGREDIENT

Titanium Dioxide 5%
Zinc Oxide 5%

PURPOSE

Sunscreen

INDICATIONS AND USAGE

■ helps prevent sunburn
■ if used as directed with other sun protection measures (see Directions), decreases the risk of skin cancer and early skin aging caused by the sun

WARNINGS

For external use only

Do not use on damaged or broken skin

When using this product keep out of eyes. Rinse with water to remove.

Stop use and ask a doctor if rash occurs

Keep out of reach of children.
If product is swallowed, get medical help or contact a Poison Control Center right away.

DOSAGE AND ADMINISTRATION

■ apply smoothly on cleansed skin
■ apply liberally 15 minutes before sun exposure
■ use a water-resistant sunscreen if swimming or sweating
■ reapply at least every 2 hours
■ children under 6 months of age: ask a doctor
■ Sun Protection Measures.
Spending time in the sun increases your risk of skin cancer and early skin aging. To decrease this risk, regularly use a sunscreen with a broad-spectrum SPF value of 15 or higher and other sun protection measures including:
■ limit time in the sun, especially from 10 a.m. – 2 p.m.
■ wear long-sleeve shirts, pants, hats, and sunglasses

CLINICAL STUDIES

■ for normal to oily skin
■ dermatologist tested
■ may stain some fabrics

STORAGE AND HANDLING

■ protect this product from excessive heat and direct sun
■ do not store at temperatures below 32°F (0°C) or above 120°F (49°C)

INACTIVE INGREDIENT

water (aqua), cyclopentasiloxane, butylene glycol, octyldodecyl neopentanoate, PEG/PPG-18/18 dimethicone, dimethicone, magnesium chloride, potassium chloride, sodium chloride, zinc chloride, lysine, tocopherol, tetrahexyldecyl ascorbate, magnesium ascorbyl phosphate, retinyl palmitate, panax ginseng root extract, ginkgo biloba leaf extract, camellia sinensis leaf extract, chamomilla recutita (matricaria) flower extract, octyldodecanol, sodium hyaluronate, phytantriol, glycerin, triethoxycaprylylsilane, boron nitride, dextrin palmitate, palmitic acid, methicone, stearic acid, aluminum hydroxide, hexylene glycol, disodium EDTA, potassium sorbate, sodium dehydroacetate, caprylyl glycol, phenoxyethanol, (+/-): iron oxides (CI 77491, CI 77492, CI 77499), titanium dioxide (CI 77891), mica